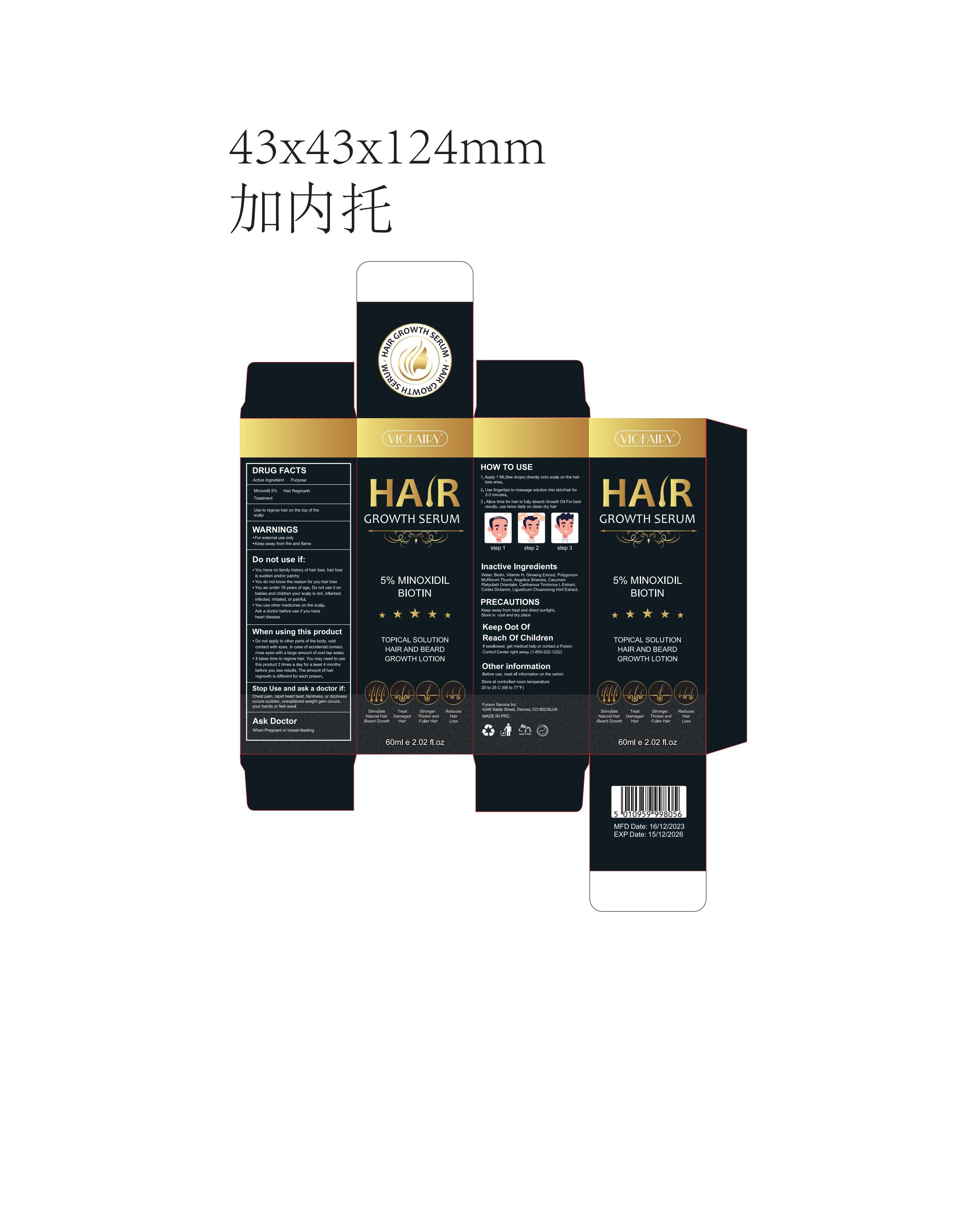 DRUG LABEL: VIOFAIRY 5% Minoxidil  Hair Growth serum
NDC: 83804-110 | Form: LIQUID
Manufacturer: Shenzhen Shandian Jingling Technology Co., Ltd.
Category: otc | Type: HUMAN OTC DRUG LABEL
Date: 20240425

ACTIVE INGREDIENTS: MINOXIDIL 5 g/100 mL
INACTIVE INGREDIENTS: VITAMIN A; ASIAN GINSENG; POLYGONATUM MULTIFLORUM ROOT; LIGUSTICUM SINENSE SUBSP. CHUANXIONG ROOT; BIOTIN; WATER; PLATYCLADUS ORIENTALIS LEAF; SAFFLOWER; CORDIA DICHOTOMA WHOLE; ANGELICA SINENSIS ROOT OIL

83804-110

Active Ingredient

Minoxidil 5%

Purpose

Hair Regrowth Treatment

Use

to regrow hair on the top of the scalp

Warnings

For external use only

Keep away from fire and flame

Avoid contact with eyes

Do not use

You have no family history of hair loss,hair loss is sudden and/or patchy

you are under 18 years of age.Do not use it on babies and children

When Using

Do not apply on other parts of the body

void contact with eyes. In case of accidental contact, rinse eyes with a large amount of cool tap water

It takes time to regrow hair. You may need to use this product 2 times a day for a least 4 months before you see results, The amount of hair regrowth is different for each person

Stop Use

chest pain, rapid heart beat, faintness, or dizziness occurs

sudden, unexplained weight gain occurs

your hands or feet swell

scalp irritation or redness occurs

Ask Doctor

When Pregnant or breast-feeding

Keep Oot Of Reach Of Children

When Pregnant or breast-feeding

Directions

1. Apply 1 ML(few drops) directly onto scalp on the hairloss area.
2. Use fingertips to massage solution into skinjhair for2-3 minutes.
3. Allow time for hair tofully absorb Growth Oil For bestresults, use twice daily on clean dry hair

Other information

Before use, read all information on the carton

Store at controlled room temperature 20 to 25 C (68 to 77°F)

Inactive ingredients

Biotin
Vitamin H
Water
Ginseng Extroct
polygonum multiflorum Thunb
Angelica Sinensis
Cacumen Platycladi Orientalis
Carthamus Tinctorius L Extract
Ligusticum Chuanxiong Hort Extract
Cortex Dictamni

Questions

service@amazonfairy.com